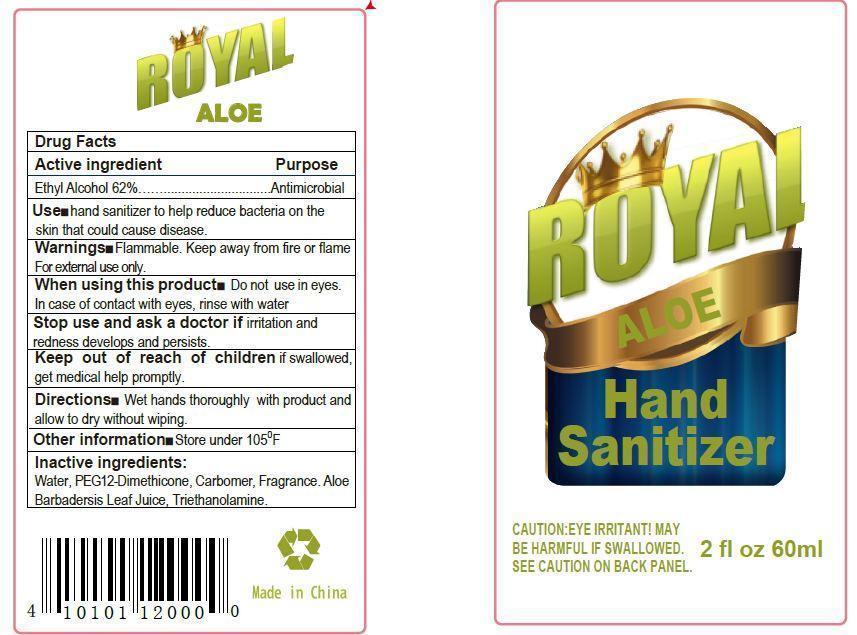 DRUG LABEL: Royal Hand Sanitizer
                
                
NDC: 55439-000 | Form: GEL
Manufacturer: GPM Investments LLC
Category: otc | Type: HUMAN OTC DRUG LABEL
Date: 20130109

ACTIVE INGREDIENTS: ALCOHOL 620 mg/1 mL
INACTIVE INGREDIENTS: WATER; ALOE VERA LEAF; TROLAMINE

Royal Hand Sanitizer

Active ingredient

Ethyl Alcohol 62 percent

Purpose

Antimicrobial

Use

hand sanitizer to help reduce bacteria on the skin that could cause disease.

Warnings

Flammable. Keep away from fire or flame
For external use only.

When using this product

Do not use in eyes.
In case of contact with eyes, rinse with water

Stop use and ask a doctor if

irritation and redness develops and persists.

Keep out of reach of children

if swallowed, get medical help promptly.

Directions

Wet hands thoroughly with product and allow to dry without wiping.

Other information

Store under 105 degrees F

Inactive ingredients

Water, PEG12-Dimethicone, Carbomer, Fragrance. Aloe Barbadersis Leaf Juice, Triethanolamine.

Package label

ROYAL ALOE Hand Sanitizer
CAUTION:EYE IRRITANT! MAY BE HARMFUL IF SWALLOWED.
SEE CAUTION ON BACK PANEL.
2 fl oz 60ml
Made in China